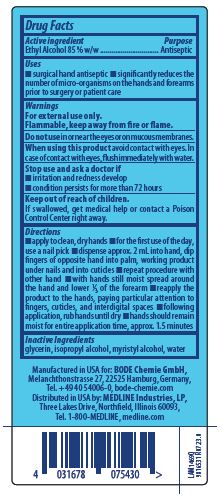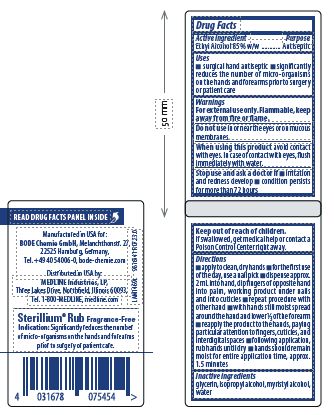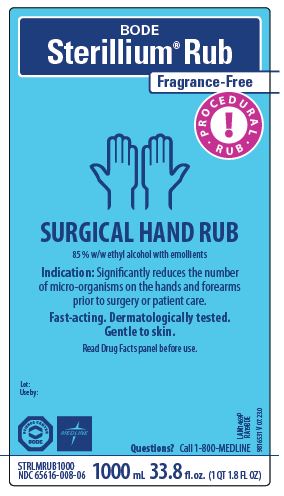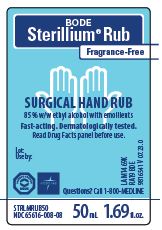 DRUG LABEL: Sterillium Rub Fragrance Free
NDC: 65616-008 | Form: LIQUID
Manufacturer: BODE Chemie GmbH
Category: otc | Type: HUMAN OTC DRUG LABEL
Date: 20250414

ACTIVE INGREDIENTS: ALCOHOL 89.5 mL/100 mL
INACTIVE INGREDIENTS: WATER; ISOPROPYL ALCOHOL; MYRISTYL ALCOHOL; GLYCERIN

Sterillium Rub Fragrance Free NDC 65616-008

Active ingredient

Ethyl Alcohol 85% w/w

Purpose

Antiseptic

Uses

- surgical hand antiseptic
- significantly reduces the number of micro-organisms on the hands and forearms prior to surgery or patient care

Warnings

For external use only.

Flammable, keep away from fire or flame.

DO NOT USE

Do not usein or near the eyes or on mucous membranes.

WHEN USING

When using this productavoid contact with eyes. In case of contact with eyes, flush immediately with water.

Stop use and ask a doctor if

- irritation and redness develop
- condition persists for more than 72 hours

Keep out of reach of children.

If swallowed, get medical help or contact a Poison Control Center right away.

Directions

- apply to clean, dry hands
- for the first use of the day, use a nail pick
- dispense approx. 2 mL into hand, dip fingers of opposite hand into palm, working product under nails and into cuticles
- repeat procedure with other hand
- with hands still moist spread around the hand and lower 1/3 of the forearm
- reapply the product to the hands, paying particular attention to fingers, cuticles, and interdigital spaces
- following application, rub hands until dry
- hands should remain moist for entire application time, approx. 1.5 minutes.

Inactive ingredients

glycerin, isopropyl alcohol,myristyl alcohol, water

PACKAGE LABEL

BODE

Sterillium Rub

Fragrance-Free

Procedural Rub

SURGICAL HAND RUB

85% w/w ethyl alcohol with emollients

Indication: Significantly reduces the number

of micro-organisms on the hands and forearms

prior to surgery or patient care.

Fast-actng. Dermatologically tested.

Gentle to skin.

Read Drug Facts panel before use.

Lot:

Use by:

Questions? Call 1-800-MEDLINE

NDC 65616-008-06

1000 mL 33.8 fl.oz.